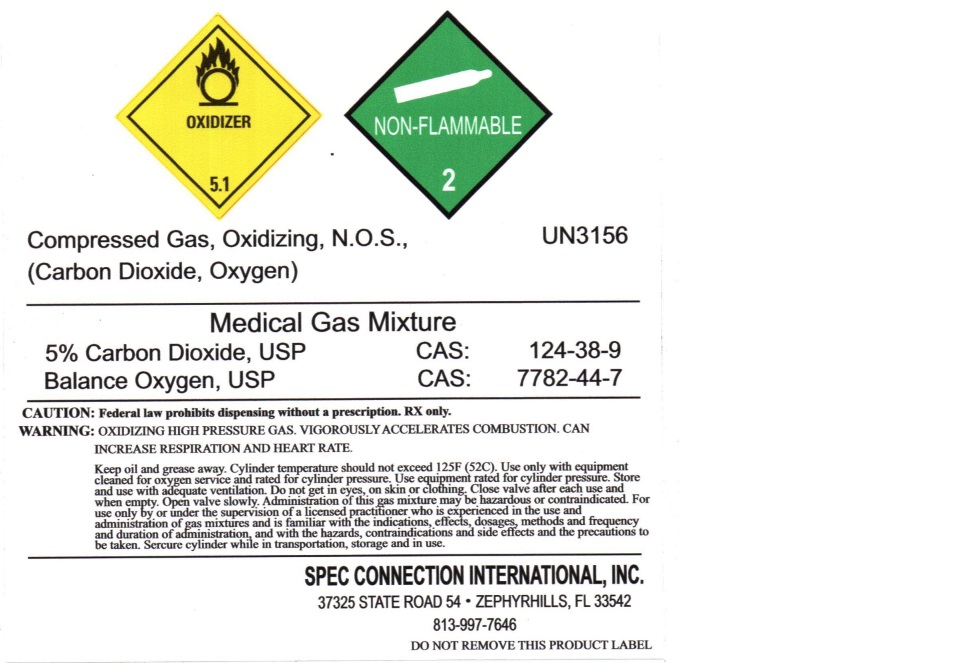 DRUG LABEL: Carbon Dioxide Oxygen Mixture
NDC: 54776-004 | Form: GAS
Manufacturer: Spec Connection International Inc
Category: prescription | Type: HUMAN PRESCRIPTION DRUG LABEL
Date: 20241119

ACTIVE INGREDIENTS: OXYGEN 800 mL/1 L
INACTIVE INGREDIENTS: CARBON DIOXIDE 200 mL/1 L

Carbon Dioxide Oxygen Mixture

PACKAGE LABEL

Compressed Gas, Oxidizing, N.O.S.,

(Carbon Dioxide, Oxygen)

Medical Gas Mixture

5 percent Carbon Dioxide, USP CAS: 124-38-9

Balance Oxygen, USP CAS: 7782-44-7

CAUTION: Federal law prohibits dispensing without a prescription. RX only.

WARNING: OXIDZING HIGH PRESSURE GAS. VIGOROUSLY ACCELERATES COMBUSTION. CAN INCREASE RESPIRATION AND HEART RATE.

Keep oil and grease away. Cylinder temperature should not exceed 125 F (52 C). Use only with equipment cleaned for oxygen service and rated for cylinder pressure. Use equipment rated for cylinder pressure. Store and use with adequate ventilation. Do not get in eyes, on skin or clothing. Close valve after each use and when empty. Open valve slowly. Administration of this gas mixture may be hazardous or contraindicated. For use only by or under the supervision of a licensed practitioner who is experienced in the use and administration of gas mixtures and is familiar with the indications, effects, dosages, methods and frequency and duration of administration, and with the hazards, contraindications and side effects and the precautions to be taken. Secure cylinder while in transportation, storage and in use.

SPEC CONNECTION INTERNATION, INC.

37325 STATE ROAD 54 ZEPHYRHILLS, FL 33542

813-997-7646

DO NOT REMOVE THIS PRODUCT LABEL